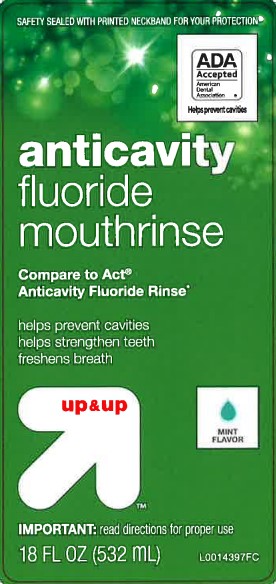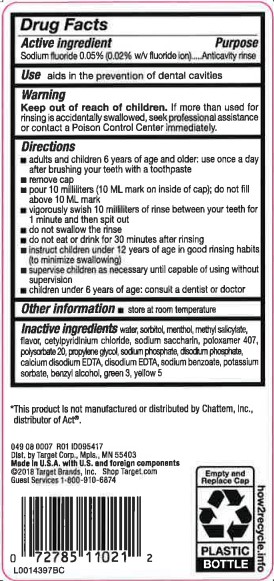 DRUG LABEL: Fluoride Mouth Rinse Anticavity
NDC: 11673-213 | Form: MOUTHWASH
Manufacturer: Target Corporation
Category: otc | Type: HUMAN OTC DRUG LABEL
Date: 20260218

ACTIVE INGREDIENTS: SODIUM FLUORIDE 0.2 mg/1 mL
INACTIVE INGREDIENTS: WATER; SORBITOL; MENTHOL; METHYL SALICYLATE; CETYLPYRIDINIUM CHLORIDE; SACCHARIN SODIUM; POLOXAMER 407; POLYSORBATE 20; PROPYLENE GLYCOL; SODIUM PHOSPHATE; SODIUM PHOSPHATE, DIBASIC, ANHYDROUS; EDETATE CALCIUM DISODIUM ANHYDROUS; EDETATE DISODIUM ANHYDROUS; SODIUM BENZOATE; POTASSIUM SORBATE; BENZYL ALCOHOL; FD&C GREEN NO. 3; FD&C YELLOW NO. 5

Up & Up 213.002/213AE rev 2
Anticavity Fluoride Rinse, Mint

Active ingredient

Sodium fluoride 0.05% (0.02% w/v fluoride ion)

Purpose

Anticavity rinse

Use

aids in the prevention of dental cavities

Warnings

for this product

Keep out of reach of children.

If more than used for rinsing is accidentally swallowed, seek professional assistance or contact a Poison Control Center immediately.

Directions

- Adults and children 6 years of age and older: use once a day after brushing your teeth with toothpaste
- remove cap
- pour 10 milliliters (10 mL mark on inside of cap); do not fill above 10 mL mark
- vigorously swish 10 milliliters of rinse between your teeth for 1 minute then spit it out
- do not swallow the rinse
- do not eat or drink for 30 minutes after rinsing
- instruct children under 12 years of age in good rinsing habits (to minimize swallowing)
- supervise children as necessary until capable of using without supervision
- children under 6 years of age: consult a dentist or doctor

Other information

- store at room temperature

Inactive ingredients

water, sorbitol, menthol, methyl salicylate, flavor, cetylpyridinium chloride, sodium saccharin, poloxamer 407, polysorbate 20, propylene glycol, sodium phosphate, disodium phosphate, calcium disodium EDTA, disodium EDTA, sodium benzoate, potassium sorbate, benzyl alcohol, green 3, yellow 5

Disclaimer

*This product is not manufactured or distributed by Chattem, Inc., distributor of Act.

ADVERSE REACTION

Dist. by Target Corp., Mpls, MN 55403

Made in U.S.A. with U.S. and foreign components

©2018 Target Brands, Inc. Shop Target.com

Guest Services 1-800-910-6874

Empty and Replace Cap

PLASTIC BOTTLE

how2recycle.info

Principal display panel

SAFETY SEALED WITH PRINTED NECKBAND FOR YOUR PROTECTION

ADA Accepted

America Dental Association

Helps prevent cavities

anticavity

fluoride

mouthrinse

Compare to Act®Anticavity Fluoride Rinse*

helps prevent cavities

helps strengthen teeth

freshens breath

up & up™

MINT FLAVOR

IMPORTANT: read directions for proper use

18 FL OZ (532 mL)